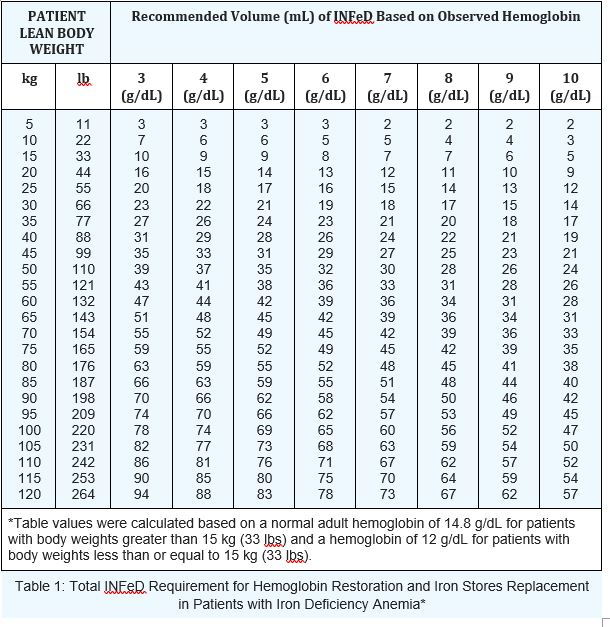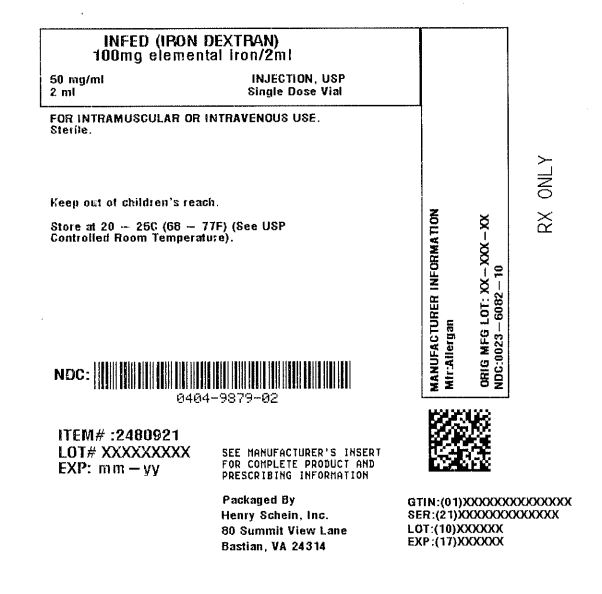 DRUG LABEL: INFED
NDC: 0404-9879 | Form: INJECTION
Manufacturer: Henry Schein, Inc.
Category: prescription | Type: HUMAN PRESCRIPTION DRUG LABEL
Date: 20251031

ACTIVE INGREDIENTS: IRON DEXTRAN 50 mg/1 mL
INACTIVE INGREDIENTS: SODIUM HYDROXIDE

HIGHLIGHTS OF PRESCRIBING INFORMATION

These highlights do not include all the information needed to use INFeD safely and effectively. See full prescribing information for INFeD.INFeD® (iron dextran injection), for intravenous or intramuscular use
Initial U.S. Approval: 1974

1 INDICATIONS AND USAGE

INFeD, an iron replacement product, is indicated for treatment of adult and pediatric patients of age 4 months and older with documented iron deficiency who have intolerance to oral iron or an unsatisfactory response to oral iron. (1)

2 DOSAGE AND ADMINISTRATION

See Full Prescribing Information for weight-based dosing and administration information. (2)

3 DOSAGE FORMS AND STRENGTHS

Injection: 100 mg/2 mL (50 mg/mL) in single-dose vials (3)

4 CONTRAINDICATIONS

Known hypersensitivity to INFeD (4)

5 WARNINGS AND PRECAUTIONS

Delayed Reactions: May occur with large intravenous doses. (5.2)
Increased Risk of Toxicity in Patients with Underlying Conditions: Monitor for toxicity in these patients. (5.3)
Iron Overload: Excessive therapy can lead to iatrogenic hemosiderosis. Do not administer to patients with iron overload. Periodically monitor hematologic and iron parameters. (5.4)

6 ADVERSE REACTIONS

Most common adverse reactions are nausea, vomiting, chest pain, backache, hypersensitivity, dyspnea, hypotension, pruritus, flushing, dizziness. (6)

To report SUSPECTED ADVERSE REACTIONS, contact Allergan at 1-800-678-1605 or FDA at 1-800-FDA-1088 or www.fda.gov/medwatch.

8 USE IN SPECIFIC POPULATIONS

Pregnancy: Risk of hypersensitivity reaction which may have serious consequences for the fetus. (8.1)

See 17 for PATIENT COUNSELING INFORMATION.

Revised: 9/2021

FULL PRESCRIBING INFORMATION

BOXED WARNING

These highlights do not include all the information needed to use INFeD safely and effectively. See full prescribing information for INFeD.

INFeD® (iron dextran injection), for intravenous or intramuscular use
Initial U.S. Approval: 1974

WARNING: RISK FOR ANAPHYLACTIC-TYPE REACTIONS
SEE FULL PRESCRIBING INFORMATION FOR COMPLETE BOXED WARNING.
Anaphylactic-type reactions, including fatalities, have been reported following the parenteral administration of iron dextran injection. (5.1)
Have resuscitation equipment and personnel trained in the detection and treatment of anaphylactic-type reactions readily available during INFeD administration.
Administer a test INFeD dose prior to the first therapeutic dose. If no signs or symptoms of anaphylactic-type reactions follow the test dose, administer the full therapeutic INFeD dose.
During all INFeD administrations, observe for signs or symptoms of anaphylactic-type reactions. Fatal reactions have been reported following the test dose of iron dextran injection. Fatal reactions have also occurred in situations where the test dose was tolerated.
Use INFeD only in patients in whom clinical and laboratory investigations have established an iron deficient state not amenable to oral iron therapy.
Patients with a history of drug allergy or multiple drug allergies may be at increased risk of anaphylactic-type reactions to INFeD. (5.3)

1 INDICATIONS AND USAGE

INFeD is indicated for treatment of adult and pediatric patients of age 4 months and older with documented iron deficiency who have intolerance to oral iron or have had an unsatisfactory response to oral iron.

2 DOSAGE AND ADMINISTRATION

2.1 Important Pre-Treatment Information
Discontinue administration of any iron-containing products prior to administration of INFeD.

Assess baseline hematologic (hemoglobin and hematocrit) and iron storage parameters (serum iron, total iron binding capacity, and percent saturation of transferrin) to monitor response to therapy.

Administer a test dose of INFeD prior to administration of therapeutic dose [see Dosage and Administration (2.4)].

2.2 Recommended Dosage for Iron Deficiency Anemia
Calculate the INFeD dose based upon Table 1 and formulas below. Continue INFeD until hemoglobin is within the normal range and iron stores are replete.

Administer daily doses of no more than 2 mL of INFeD until the total required dose is administered. Monitor response to therapy by evaluating hematologic parameters (hemoglobin and hematocrit) and iron storage parameters (serum iron, total iron binding capacity, and percent saturation of transferrin). Iron storage parameters may improve prior to hematologic parameters. Serum ferritin may not be an accurate measure of body iron stores in patients on chronic dialysis.

Table 1: Total INFeD Requirement for Hemoglobin Restoration and Iron Stores Replacement in Patients with Iron Deficiency Anemia*

Alternatively, the total dose may be calculated using the formulas below:

Adults and Children over 15 kg (33 lbs)

Dose (mL) = 0.0442 (Desired Hb - Observed Hb) x LBW + (0.26 x LBW)

Based on:

• Desired Hb = the target hemoglobin in g/dL [Normal hemoglobin (males and females) for body weight over 15 kg (33 lbs) is 14.8 g/dL.]

• Observed Hb = the patient’s current hemoglobin in g/dL

• LBW = Lean body weight in kg [A patient’s lean body weight (or actual body weight if less than lean body weight) should be utilized when determining dosage.]
• For males: LBW = 50 kg + 2.3 kg for each inch of patient’s height over 5 feet
• For females: LBW = 45.5 kg + 2.3 kg for each inch of patient’s height over 5 feet
• To calculate a patient's weight in kg when lbs are known:

Weight in Kg

Children 5 to 15 kg (11 to 33 lbs)

Otherwise, the total dose may be calculated using the formula below:

Dose (mL) = 0.0442 (Desired Hb - Observed Hb) x W + (0.26 x W)

Based on:

• Desired Hb = the target hemoglobin in g/dL [Normal hemoglobin for children with body weight of 15 kg (33 lbs) or less is 12 g/dL.]

• W = body weight in kg
• To calculate a patient's weight in kg when lbs are known:

Weight in Kg

2.3 Recommended Dosage of Iron Replacement for Blood Loss
Calculate the INFeD dose based upon the formula below which is based upon the approximate amount of blood loss and pretreatment hematocrit.

The formula is based on the approximation that 1 mL of normocytic, normochromic red cells contains 1 mg of elemental iron.

INFeD Dose (in mL) = [Blood loss (in mL) x hematocrit] ÷ 50 mg/mL

Example: Blood loss of 500 mL with 20% hematocrit

Replacement Iron = 500 x 0.20 = 100 mg

INFeD dose volume = INFeD dose volume

2.4 Administration
The total volume of INFeD required for the treatment of iron deficiency anemia is determined from Table 1 or the appropriate formula listed [see Dosage and Administration (2.2)].

The total volume of INFeD required for the treatment of iron replacement for blood loss is determined from an appropriate formula listed [see Dosage and Administration (2.3)].

NOTE: Do not mix INFeD with other medications or add to parenteral nutrition solutions for intravenous infusion.

Parenteral drug products should be inspected visually for particulate matter and discoloration prior to administration, whenever the solution and container permit.

Discard unused portion.

Intravenous Injection

Test Dose

Prior to the first intravenous INFeD therapeutic dose, administer an intravenous test dose of 0.5 mL [see BOXED WARNING and Warnings and Precautions (5.1)]. Administer the test dose at a gradual rate over at least 30 seconds. Delay administration of the initial therapeutic INFeD dose until 1 hour or more after the test dose. If a hypersensitivity reaction occurs with the test dose, manage medically and do not administer further doses of INFeD.

INFeD is given undiluted at a slow gradual rate not to exceed 50 mg (1 mL) per minute.

The maximum daily dose of INFeD should not exceed 2 mL.

Intramuscular Injection

Test Dose

Prior to the first intramuscular INFeD therapeutic dose, administer an intramuscular test dose of 0.5 mL [see BOXED WARNING and Warnings and Precautions (5.1)]. Administer the test dose at a gradual rate over at least 30 seconds into the buttock. Delay administration of the initial therapeutic INFeD dose until 1 hour or more after the test dose. If a hypersensitivity reaction occurs with the test dose, manage medically and do not administer further doses of INFeD.

If no adverse reactions are observed, INFeD can be given according to the following schedule until the calculated total required dose has been reached. Each day’s dose should not exceed 0.5 mL (25 mg of iron) for infants with body weight under 5 kg (11 lbs); 1 mL (50 mg of iron) for children with body weight under 10 kg (22 lbs); and 2 mL (100 mg of iron) for other patients.

The maximum daily dose of INFeD should not exceed 2 mL.

INFeD should be injected only into the muscle mass of the upper outer quadrant of the buttock - never into the arm or other exposed areas - and should be injected deeply, with a 2-inch or 3-inch 19 or 20 gauge needle. If the patient is standing, he/she should be bearing his/her weight on the leg opposite the injection site, or if in bed, he/she should be in the lateral position with injection site uppermost. To avoid injection or leakage into the subcutaneous tissue, a Z-track technique (displacement of the skin laterally prior to injection) is recommended.

3 DOSAGE FORMS AND STRENGTHS

Injection: 100 mg/2 mL (50 mg/1 mL), dark brown, slightly viscous, sterile solution in single-dose vials

4 CONTRAINDICATIONS

INFeD is contraindicated in patients who have demonstrated a previous hypersensitivity to iron dextran [see Warnings and Precautions (5.1)].

5 WARNINGS AND PRECAUTIONS

5.1 Hypersensitivity Reactions
Serious hypersensitivity reactions, including anaphylactic-type reactions, some of which have been life-threatening and fatal, have been reported following the parenteral administration of iron dextran products, including INFeD. Such reactions have been generally characterized by sudden onset of respiratory difficulty and/or cardiovascular collapse. Fatal reactions have been reported following the test dose of iron dextran and have also occurred in situations where the test dose was tolerated.

Administer only in a setting where resuscitation equipment and medications are available. Administer a test dose of INFeD prior to the first therapeutic dose [see Dosage and Administration (2.4)]. Observe patients for at least one hour after the test dose before administering the remainder of the initial therapeutic dose. During all INFeD administrations, observe patients for signs or symptoms of anaphylactic-type reactions. Use INFeD only in patients in whom clinical and laboratory investigations have established an iron deficient state not amenable to oral iron therapy.

The factors that affect the risk for anaphylactic-type reactions to iron dextran products are not fully known but limited clinical data suggest the risk may be increased among patients with a history of drug allergy or multiple drug allergies. Additionally, concomitant use of angiotensin-converting enzyme inhibitor drugs may increase the risk for reactions to an iron dextran product. The extent of risk for anaphylactic-type reactions following exposure to any specific iron dextran product is unknown and may vary among the products.

If hypersensitivity reactions occur during administration, stop INFeD immediately and manage reaction medically.

5.2 Delayed Reactions
Large intravenous doses, such as used with total dose infusions (TDI), have been associated with an increased incidence of adverse reactions. The adverse reactions are frequently delayed (1 to 2 days) reactions typified by one or more of the following symptoms: arthralgia, backache, chills, dizziness, moderate to high fever, headache, malaise, myalgia, nausea, and vomiting. The onset is usually 24 to 48 hours after administration and symptoms generally subside within 3 to 4 days. The etiology of these reactions is not known. Do not exceed a total daily dose of 2 mL undiluted INFeD.

5.3 Increased Risk of Toxicity in Patients with Underlying Conditions
Monitor for iron toxicity when INFeD is used in patients with serious impairment of liver function. It should not be used during the acute phase of infectious kidney disease.

Adverse reactions experienced following administration of INFeD may exacerbate cardiovascular complications in patients with pre-existing cardiovascular disease.

Patients with rheumatoid arthritis may have an acute exacerbation of joint pain and swelling following the administration of INFeD.

Patients with a history of significant allergies and/or asthma may have an increased risk of hypersensitivity reactions [see Dosage and Administration (5.1)].

5.4 Iron Overload
Excessive therapy with parenteral iron can lead to excess storage of iron with the possibility of iatrogenic hemosiderosis. All adult and pediatric patients receiving INFeD require periodic monitoring of hematologic and iron parameters (hemoglobin, hematocrit, serum ferritin and transferrin saturation). Do not administer INFeD to patients with evidence of iron overload.

6 ADVERSE REACTIONS

The following clinically significant adverse reactions are described elsewhere in the labeling:

Hypersensitivity Reactions [see Warnings and Precautions (5.1)]
Delayed Reactions [see Warnings and Precautions (5.2)]
Increased Risk of Toxicity in Patients with Underlying Conditions [see Warnings and Precautions (5.3)]
Iron Overload [see Warnings and Precautions (5.4)]
Fetal bradycardia [see Use in Specific Populations (8.1)]
The following adverse reactions associated with the use of INFeD were identified in clinical studies or postmarketing reports. Because some of these reactions were reported voluntarily from a population of uncertain size, it is not always possible to reliably estimate their frequency or establish a causal relationship to drug exposure.

Blood and lymphatic system disorders: Leukocytosis, lymphadenopathy.

Cardiac disorders: Cardiac arrest, tachycardia, bradycardia, arrhythmias.

Gastrointestinal disorders: Abdominal pain, nausea, vomiting, diarrhea.

General disorders and administration site conditions: chest pain, chest tightness, weakness, malaise, febrile episodes, chills, shivering, sterile abscess, atrophy/fibrosis (intramuscular injection site), brown skin and/or underlying tissue discoloration (staining), soreness or pain at or near intramuscular injection sites, swelling, inflammation.

Musculoskeletal and connective tissue disorders: Arthralgia, arthritis (may represent reactivation in patients with quiescent rheumatoid arthritis – [see Warnings and Precautions (5.3)], myalgia, backache.

Nervous system disorders: Convulsions, seizures, syncope, headache, unresponsiveness, paresthesia, dizziness, numbness, unconsciousness, altered taste.

Psychiatric disorders: Disorientation

Respiratory, thoracic and mediastinal disorders: Respiratory arrest, dyspnea, bronchospasm, wheezing.

Renal and urinary disorders: Hematuria.

Skin and subcutaneous disorders: Urticaria, pruritus, purpura, rash, sweating.

Vascular disorders: Cyanosis, shock, hypertension, hypotension, flushing (flushing and hypotension may occur from too rapid injections by the intravenous route), local phlebitis at or near intravenous injection site.

7 DRUG INTERACTIONS

7.1 Drug/Laboratory Test Interactions
Drug interactions involving INFeD have not been studied.

Concomitant use of angiotensin-converting enzyme inhibitor drugs may increase the risk for anaphylactic-type reactions to an iron dextran product.

Large doses of iron dextran (5 mL or more) have been reported to give a brown color to serum from a blood sample drawn 4 hours after administration.

INFeD may cause falsely elevated values of serum bilirubin and falsely decreased values of serum calcium.

Serum iron determinations (especially by colorimetric assays) may not be meaningful for 3 weeks following the administration of INFeD.

Examination of the bone marrow for iron stores may not be meaningful for prolonged periods following iron dextran therapy because residual iron dextran may remain in the reticuloendothelial cells.

Bone scans involving 99m Tc-diphosphonate have been reported to show a dense, crescentic area of activity in the buttocks, following the contour of the iliac crest, 1 to 6 days after intramuscular injections of INFeD.

Bone scans with 99m Tc-labeled bone seeking agents, in the presence of high serum ferritin levels or following INFeD infusions, have been reported to show reduction of bony uptake, marked renal activity, and excessive blood pool and soft tissue accumulation.

8 USE IN SPECIFIC POPULATIONS

8.1 Pregnancy
Risk Summary
Parenteral iron administration may be associated with hypersensitivity reactions [see Warnings and Precautions (5.1)], which may have serious consequences, such as fetal bradycardia (see Clinical Considerations). Advise pregnant persons of the potential risk to the fetus. Available data from postmarketing reports with iron dextran use in pregnancy are insufficient to assess the risk of major birth defects or miscarriage. There are risks to the pregnant person and fetus associated with untreated iron deficiency anemia in pregnancy (see Clinical Considerations). Iron dextran has been shown to be teratogenic and embryocidal in mice, rats, rabbits, dogs, and monkeys when given in doses of about 3 times the maximum human dose.

The estimated background risk of major birth defects and miscarriage for the indicated population is unknown. All pregnancies have a background risk of birth defects, loss, or other adverse outcomes. In the U.S. general population, the estimated background risk of major birth defects and miscarriage in clinically recognized pregnancies is 2-4% and 15-20%, respectively.

Clinical Considerations
Disease-Associated Maternal and/or Embryo/Fetal Risk
Untreated iron deficiency anemia (IDA) in pregnancy is associated with adverse maternal outcomes such as post-partum anemia. Adverse pregnancy outcomes associated with IDA include increased risk for preterm delivery and low birth weight.

Fetal/Neonatal Adverse Reactions
Severe adverse reactions including circulatory failure (severe hypotension, shock including in the context of anaphylactic reaction) may occur in pregnant persons with intravenous iron administration (such as INFeD) which may have serious consequences on the fetus such as fetal bradycardia, especially during the second and third trimester.

Data
Animal Data
No consistent adverse fetal effects were observed in mice, rats, rabbits, dogs, and monkeys at doses of 50 mg iron/kg or less. Fetal and maternal toxicity has been reported in monkeys at a total intravenous dose of 90 mg iron/kg over a 14 day period. Similar effects were observed in mice and rats on administration of a single dose of 125 mg iron/kg. Fetal abnormalities in rats and dogs were observed at doses of 250 mg iron/kg and higher. The animals used in these tests were not iron deficient.

8.2 Lactation
Risk Summary
Trace amounts of unmetabolized iron dextran are present in human milk. There are no data on the effects of iron dextran in breastfed infants or effects on milk production. The development and health benefits of breastfeeding should be considered along with the mother’s clinical need for INFeD in addition to any potential adverse effects on the breastfed child from the drug or from the underlying maternal condition.

8.4 Pediatric Use
INFeD is not recommended for use in infants under 4 months of age [see Dosage and Administration (2.2)].

Reports in the literature from countries outside the United States (in particular, New Zealand) have suggested that the use of intramuscular iron dextran in neonates has been associated with an increased incidence of gram-negative sepsis, primarily due to E. Coli.

10 OVERDOSAGE

Excessive dosages of INFeD may lead to accumulation of iron in storage sites potentially leading to hemosiderosis. Do not administer INFeD to patients with iron overload [see Warnings and Precautions (5.4)]. INFeD is not removed by hemodialysis [see Clinical Pharmacology (12.3)].

11 DESCRIPTION

INFeD (iron dextran injection USP) is an iron replacement product provided as a dark brown, slightly viscous sterile liquid complex of ferric hydroxide and dextran for intravenous or intramuscular use.

Each mL contains the equivalent of 50 mg of elemental iron (as an iron dextran complex), approximately 0.9% sodium chloride, in water for injection. Sodium hydroxide and/or hydrochloric acid may have been used to adjust pH. The pH of the solution is between 4.5 to 7.0.

12 CLINICAL PHARMACOLOGY

12.1 Mechanism of Action
The circulating iron released from iron dextran, which is subject to physiological control, replenishes hemoglobin and depleted iron stores.

12.2 Pharmacodynamics
Changes in serum ferritin levels represent the changes in calculated cellular non-heme iron levels. After administration of iron dextran, evidence of a therapeutic response can be seen as an increase in the reticulocyte count.

12.3 Pharmacokinetics
Following intramuscular injection, INFeD is absorbed within 72 hours with any remaining iron absorbed over the ensuing 3 to 4 weeks. Various studies involving intravenously administered 59Fe iron dextran to iron deficient subjects, some of whom had coexisting disease, have yielded half-life values ranging from 5 hours to more than 20 hours. The 5 hour value was determined for 59Fe iron dextran from a study that used laboratory methods to separate the circulating 59Fe iron dextran from the transferrin bound 59Fe. The 20 hour value reflects a half-life determined by measuring total 59Fe, both circulating and bound. It should be understood that these half-life values do not represent clearance of iron from the body. Serum ferritin peaks approximately 7 to 9 days after an intravenous dose of INFeD and returns to baseline after about 3 weeks.

Absorption
Following intramuscular administration, INFeD is absorbed from the injection site into the capillaries and the lymphatic system.

Distribution
The circulating iron is bound to the available protein moieties to form hemosiderin or ferritin, or to a lesser extent to transferrin.

Elimination
The half-life of free iron in the plasma circulation is approximately 5 hours. The half-life of total iron, including both circulating and bound, is approximately 20 hours. These half-life values do not represent clearance of iron from the body.

Metabolism
Following administration of INFeD, circulating iron dextran is split by the cells of the reticuloendothelial system into its components of iron and dextran.

Excretion
Negligible amounts of iron are lost via the urinary or alimentary pathways after administration of iron dextran. Dextran, a polyglucose, is either metabolized or excreted.

Specific Populations
Patients with Renal Impairment
In vitro studies have shown that removal of iron dextran by dialysis is negligible. Six different dialyzer membranes were investigated (polysulfone, cuprophane, cellulose acetate, cellulose triacetate, polymethylmethacrylate and polyacrylonitrile), including those considered high efficiency and high flux.

13 NONCLINICAL TOXICOLOGY

13.1 Carcinogenesis, Mutagenesis, Impairment of Fertility
Carcinogenesis
The intramuscular injection of iron-carbohydrate complexes may be associated with an increased risk of carcinogenesis. In mice, rats, rabbits, and possibly hamsters, it has been demonstrated that these complexes may produce sarcoma following repeated administration of large or small doses of iron-carbohydrate complexes at a single injection site. There have been several reports in the literature describing tumors at the injection site in humans who had previously received intramuscular injections of iron-carbohydrate complexes.

16 HOW SUPPLIED/STORAGE AND HANDLING

16.1 How Supplied
INFeD (iron dextran injection USP) containing 50 mg of elemental iron per mL, is available as a dark brown, slightly viscous, sterile solution in 2 mL single-dose amber vials in cartons of 10 (NDC 0023-6082-10).

Product repackaged by: Henry Schein, Inc., Bastian, VA 24314
From Original Manufacturer/Distributor's NDC and Unit of Sale | To Henry Schein Repackaged Product NDC and Unit of Sale | Total Strength/Total Volume (Concentration) per unit
NDC 0023-6082-10 2 mL single dose amber vial in cartons of 10 | NDC 0404-9879-02 1 2mL single dose vial in a bag (Vial bears NDC 0023-6082-10) | 50 mg of elemental iron per mL

16.2 Stability and Storage
Store at 20°C to 25°C (68°F to 77°F); excursions permitted to 15°C to 30°C (59°F to 86°F). [See USP Controlled Room Temperature].

17 PATIENT COUNSELING

Hypersensitivity Reactions
Question patients regarding any prior history of reactions to parenteral iron products. Advise patients to immediately report any symptoms of hypersensitivity that develop during and following INFeD administration such as arthralgia, backache, chills, dizziness, moderate to high fever, headache, malaise, myalgia, nausea, and vomiting [see Warnings and Precautions (5.1)].

Delayed Reactions
Advise patients that delayed reactions can occur and that these must be reported to their healthcare provider immediately [see Warnings and Precautions (5.2)].

Increased Risk of Toxicity in Patients with Underlying Conditions
Advise patients to inform their healthcare provider if any liver impairment is identified as this may cause iron toxicity. Advise patients to consult their healthcare provider should they start to show symptoms of acute kidney infection as INFeD should not be used [see Warnings and Precautions (5.3)].

Advise patients with pre-existing cardiovascular disease and rheumatoid arthritis that INFeD administration may exacerbate symptoms and to contact their healthcare provider if any symptoms occur [see Warnings and Precautions (5.3)].

Advise patients with history of significant allergies and/or asthma to inform their healthcare provider as the risk of hypersensitivity reactions may be increased [see Warnings and Precautions (5.3)].

Iron Overload
Advise the patient to consult a healthcare provider before taking any other iron containing products as this may cause serious side effects [see Warnings and Precautions (5.4)].

Pregnancy
Advise pregnant persons about the risk of hypersensitivity reactions which may have serious consequences for the fetus [see Use in Specific Populations (8.1)].

For all medical inquiries contact:
Allergan
Medical Communications
1-800-678-1605

Manufactured By:
Patheon Italia S.p.A.
Ferentino, Italy 03013

Distributed By:
Allergan USA, Inc.
Madison, NJ 07940

© 2021 Allergan. All rights reserved.
INFeD® is a registered trademark of Allergan Sales, LLC.

v5.0USPI6082